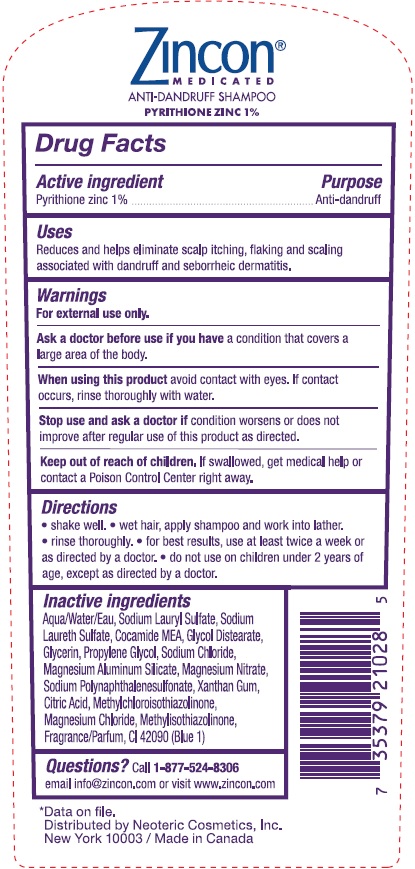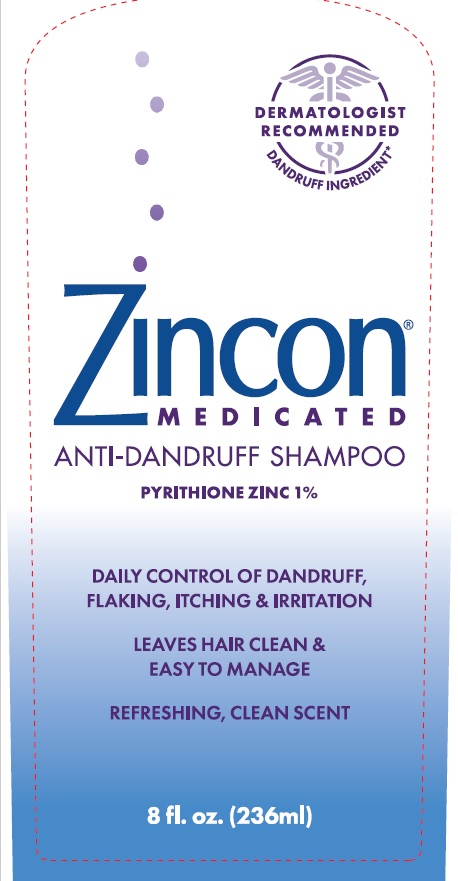 DRUG LABEL: Zincon Medicated Anti-Dandruff
NDC: 62673-017 | Form: SHAMPOO
Manufacturer: Neoteric Cosmetics, Inc.
Category: otc | Type: HUMAN OTC DRUG LABEL
Date: 20250123

ACTIVE INGREDIENTS: PYRITHIONE ZINC 0.01 g/1 mL
INACTIVE INGREDIENTS: GLYCERIN; FORMALDEHYDE/SODIUM NAPHTHALENESULFONATE COPOLYMER (3000 MW); MAGNESIUM CHLORIDE; MAGNESIUM ALUMINUM SILICATE; XANTHAN GUM; MAGNESIUM NITRATE; CITRIC ACID MONOHYDRATE; COCO MONOETHANOLAMIDE; WATER; FD&C BLUE NO. 1; GLYCOL DISTEARATE; METHYLCHLOROISOTHIAZOLINONE; METHYLISOTHIAZOLINONE; PROPYLENE GLYCOL; SODIUM CHLORIDE; SODIUM LAURETH SULFATE; SODIUM LAURYL SULFATE

Zincon Medicated Anti-Dandruff Shampoo 4oz

Drug Facts

Active Ingredient

Pyrithione zinc 1%

Purpose

Anti-dandruff

Uses

Reduces and helps eliminate scalp itching, flaking and scaling associated with dandruff and seborrheic dermatitis.

Warnings:

For external use only.

Ask a doctor before use if you

have a condition that covers a large area of the body.

When using this product

avoid contact with eyes. If contact occurs, rinse thoroughly with water.

Stop use and ask a doctor if:

condition worsens or does not improve after regular use of this product as directed.

Keep out of reach of children:

If swallowed, get medical help or contact a Poison Control Center right away.

Directions:

- Shake well
- Wet hair, apply shampoo and work into lather
- Rinse thoroughly
- For best results, use at least twice a week or as directed by a doctor
- Do not use on children under 2 years of age, except as directed by a doctor

Inactive Ingredients

Aqua/Water/Eau, Sodium Lauryl Sulfate, Sodium Laureth Sulfate, Cocamide MEA, Glycol Distearate, Glycerin, Propylene Glycol, Sodium Chloride, Magnesium Aluminum Silicate, Magnesium Nitrate, Sodium Polynaphthalenesulfonate, Xanthan gum, Citric Acid, Methylchloroisothiazolinone, Magnesium Chloride, Methylisothiazolinone, Fragrance/Parfum, CI 42090 (Blue 1)

Questions?

Call 1-877-524-8306

email info@zincon.com or visit www.zincon.com

Zincon® MEDICATED

ANTI-DANDRUFF SHAMPOO

PYRITHIONE ZINC 1%

Distributed by Neoteric Cosmetics, Inc.

New York 10003 / Made in Canada

PACKAGE LABEL

ZINCON®
MEDICATED
ANTI-DANDRUFF SHAMPOO

Pyrithione Zinc 1%

DAILY CONTROL OF DANDRUFF, FLAKING, ITCHING & IRRITATION

LEAVES HAIR CLEAN & EASY TO MANAGE

REFRESHING, CLEAN SCENT

8 fl.oz. (236 ml)